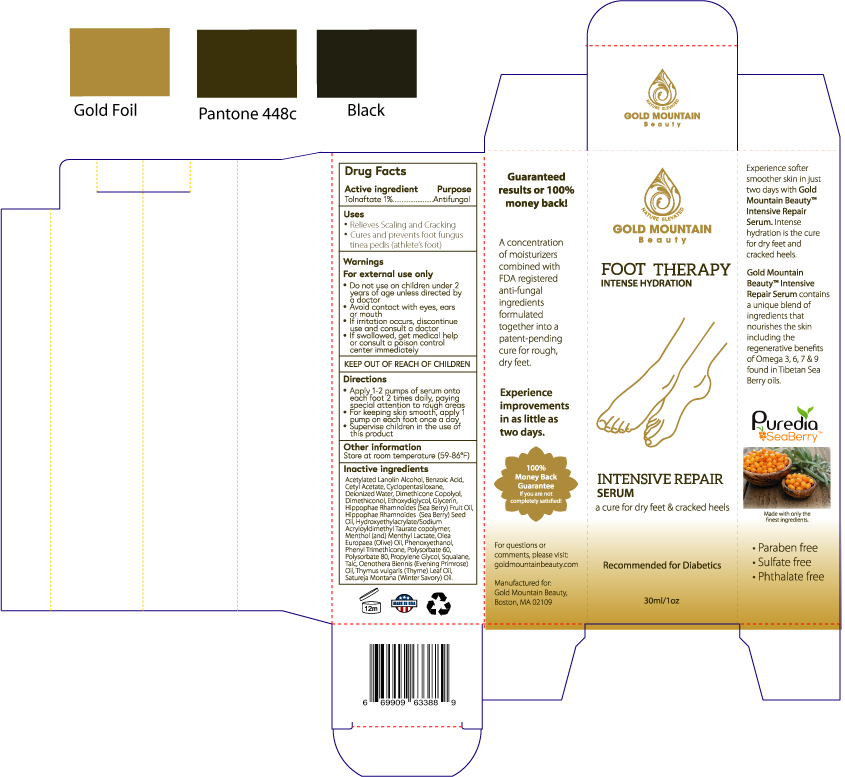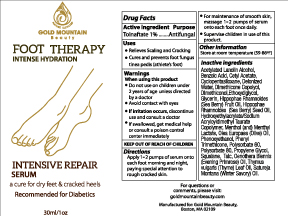 DRUG LABEL: Gold Mountain Beauty Intensive Repair Serum
NDC: 76348-418 | Form: LOTION
Manufacturer: Renu Laboratories, Inc.
Category: otc | Type: HUMAN OTC DRUG LABEL
Date: 20220114

ACTIVE INGREDIENTS: TOLNAFTATE 2.8 g/28 g
INACTIVE INGREDIENTS: CETYL ACETATE; 2-HYDROXYETHYL ACRYLATE; POLYSORBATE 60; BENZOIC ACID; TALC; HIPPOPHAE RHAMNOIDES FRUIT OIL; CYCLOMETHICONE; POLYSORBATE 80; MENTHYL LACTATE, (-)-; WATER; PHENOXYETHANOL; OLIVE OIL; SQUALANE; DEHYDROACETIC ACID; HIPPOPHAE RHAMNOIDES SEED OIL; MENTHOL; DIETHYLENE GLYCOL MONOETHYL ETHER; PROPYLENE GLYCOL; GLYCERIN; DIMETHICONOL (2000 CST); PHENYL TRIMETHICONE; ACETYLATED LANOLIN ALCOHOLS

GOLD MOUNTAIN BEAUTY
FOOT THERAPY
INTENSIVE REPAIR SERUM

Active Ingredient

Tolnaftate 1%

Purpose

Antifungal

Uses

Effectively relieves cracking, scaling and soreness accompanying fungus (tinea pedis)

- Relieves Scaling and Cracking
- Cures and prevents foot fungus tinea pedis (athlete's foot)

Warnings

For external use only

- Avoid contact with eyes, ears or mouth
- If irritation occurs, discontinue use and consult a doctor
- If swallowed, get medical help or consult a poison control center immediately

- Do not use on children under 2 years of age unless directed by a doctor

STOP USE

- If irritation occurs, discontinue use and consult a doctor

Directions

Apply 1-2 pumps of serum onto each foot 2 times daily, paying special attention to rough areas.
For keeping skin smooth, apply 1 pump on each foot once a day
Supervise children in the use of this product

Other information

Store at room temperature (59 - 86 degrees F)

Inactive ingredients

Acetylated Lanolin Alcohol, Benzoic Acid, Cetyl Acetate, Cyclopentasiloane,

Deionized Water, Dimethicone Copolyl, Dimethiconol, Ethoxydiglycol, Glycerin,

Hippophae Rhamnoides (Sea Berry) Fruit Oil, Hippophae Rhamnoides (Sea Berry) Seed Oil,

Hydroxyethylacrylate/Sodium Acryloyldimethyl Taurate copolymer, Menthol (and) Menthyl Lactate,

Olea Europaea (Olive) Oil, Phenoxyethanol, Phenyl Trimethicone, Polysorbate 60, Polysorbate 80,

Propylene Glycol, Squalane, Talc.

For questions or comments, please visit:

goldmountainbeauty.com

KEEP OUT OF REACH OF CHILDREN